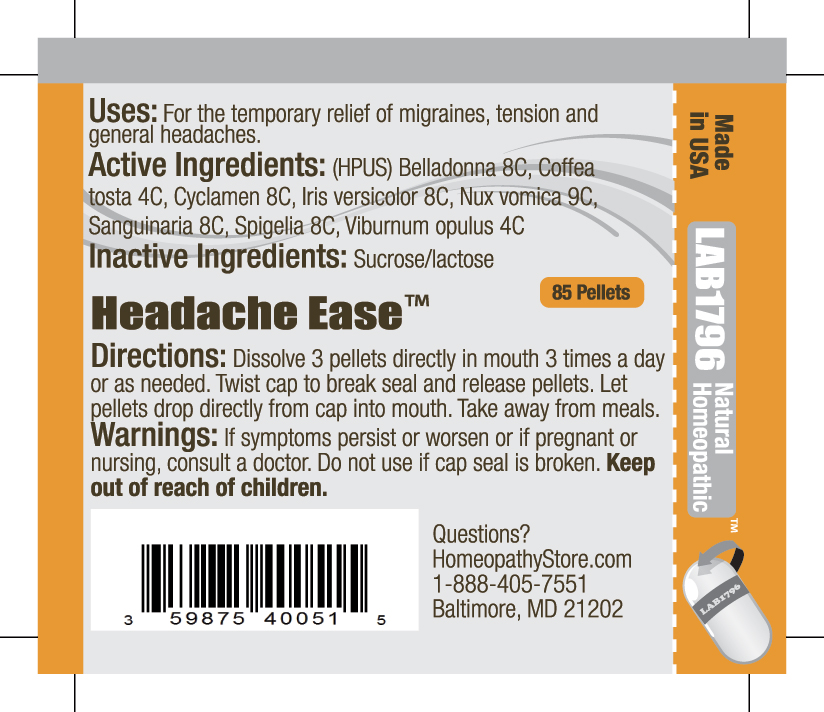 DRUG LABEL: Lab1796 Headache Ease
NDC: 59875-4005 | Form: PELLET
Manufacturer: HomeopathyStore.com
Category: homeopathic | Type: HUMAN OTC DRUG LABEL
Date: 20110801

ACTIVE INGREDIENTS: ATROPA BELLADONNA 8 [hp_C]/1 1; CYCLAMEN PURPURASCENS TUBER 8 [hp_C]/1 1; COFFEE BEAN 4 [hp_C]/1 1; IRIS VERSICOLOR ROOT 8 [hp_C]/1 1; STRYCHNOS NUX-VOMICA SEED 9 [hp_C]/1 1; SANGUINARIA CANADENSIS ROOT 8 [hp_C]/1 1; SPIGELIA MARILANDICA ROOT 8 [hp_C]/1 1; VIBURNUM OPULUS BARK 4 [hp_C]/1 1
INACTIVE INGREDIENTS: SUCROSE; LACTOSE

Headache Ease

Uses:

For the temporary relief of migraines, tension and general headaches.

Active Ingredients:

(HPUS) Belladonna 8C, Cyclamen 8C, Coffea tosta 4C, Iris versicolor 8C, Nux vomica 9C, Sanguinaria 8C, Spigelia 8C, Viburnum opulus 4C

Inactive Ingredients:

Sucrose/lactose

Directions:

DOSAGE AND ADMINISTRATION

Dissolve 3 pellets directly in mouth 3 times a day or as needed. Twist cap to break seal and release pellets. Let pellets drop directly from cap into mouth. Take away from meals.

Warnings:

If symptoms persist or worsen or if pregnant or nursing, consult a doctor. Do not use if cap seal is broken.

Keep out of reach of children.